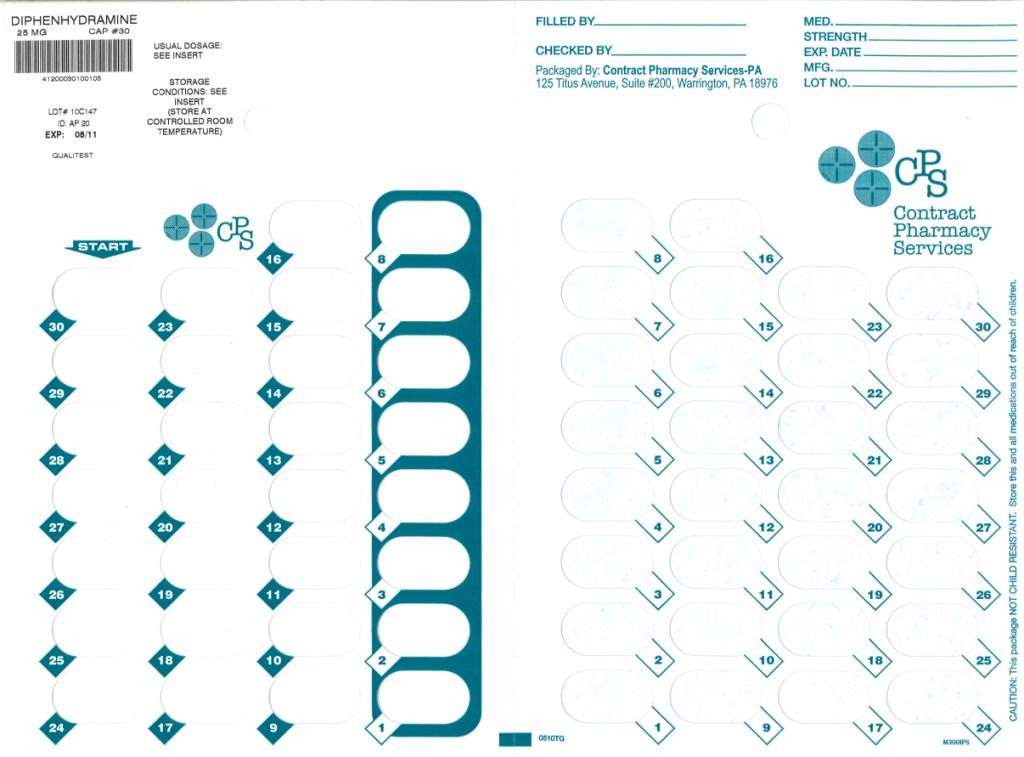 DRUG LABEL: DIPHENHYDRAMINE HYDROCHLORIDE
NDC: 67046-124 | Form: CAPSULE
Manufacturer: Contract Pharmacy Services-PA
Category: otc | Type: HUMAN OTC DRUG LABEL
Date: 20100830

ACTIVE INGREDIENTS: DIPHENHYDRAMINE HYDROCHLORIDE 25 mg/1 1
INACTIVE INGREDIENTS: BENZYL ALCOHOL; BUTYLPARABEN; D&C RED NO. 28; FD&C BLUE NO. 1; FD&C RED NO. 40; GELATIN; LACTOSE; MAGNESIUM STEARATE; METHYLPARABEN; POLYSORBATE 80; PROPYLPARABEN; SODIUM LAURYL SULFATE

Diphenhydramine Hydrochloride Capsules

ACTIVE INGREDIENT (IN EACH CAPSULE)

Diphenhydramine Hydrochloride 25 mg

PURPOSE

Antihistamine

USES

Temporarily relieves these symptoms due to hay fever or other upper respiratory allergies and common cold, sneezing, runny nose, itchy, watery eyes, itchy throat and nose.

WARNINGS

Ask a doctor before use if you have glaucoma, a breathing problem such as emphysema or chronic bronchitis, trouble urinating due to an enlarged prostate gland.

Ask a doctor before use if you have

glaucoma, a breathing problem such as emphysema or chronic bronchitis, trouble urinating due to an enlarged prostate gland.

Ask a doctor or pharmacist before use if you are

taking taking tranquilizers or sedative.

When using this product

you may get drowsy; avoid alcoholic drinks. Alcohol, sedatives and tranquilizers may increase drowsiness. Be careful when driving a motor vehicle or operating machinery. Excitability may occur, especially in children. Do not use any other products containing diphenhydramine.

If pregnant or breast-feeding, ask a health professional before use.

Keep out of reach of children.

In case of overdose, get medical help or contact a Poison Control Center right away. (1-800-222-1222

DIRECTIONS

Adults and children 12 years and over: take 25 to 50 mg (1 to 2 capsule) every 4 to 6 hours; not more than 12 capsules in 24 hours.

Children 6 years to 12 years of age: take 25 mg (1 capsule) every 4 to 6 hours; not more than 6 capsules in 24 hours.

Children under 6 years of age: ask a doctor

OTHER INFORMATION

Store at controlled room temperature 59-86 degrees F.

INACTIVE INGREDIENTS

benzyl alcohol, butylparaben, D&C red #28, edible black ink, FD&C blue #1, FD&C red #40, gelatin, lactose, magnesium stearate, methylparaben, polysorbate 80, propylparaben, sodium lauryl sulfate.

QUESTIONS OR COMMENTS?

Distributed by:

Qualitest Pharmaceuticals, Inc.

130 Vintage Drive

Huntsville, AL 35811

Repackaged by:
Contract Pharmacy Services-PA
125 Titus Ave Suite 200
Warrington, PA 18976 USA

Original--08/2010--NJW

Package Label

25 mg Capsules